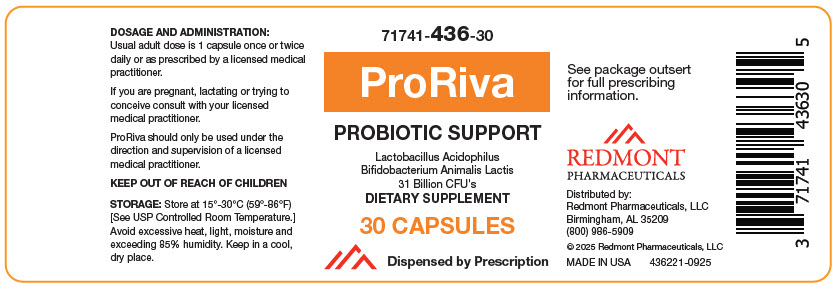 DRUG LABEL: ProRiva
NDC: 71741-436 | Form: CAPSULE
Manufacturer: Redmont Pharmaceuticals, LLC
Category: other | Type: DIETARY SUPPLEMENT
Date: 20250829

ACTIVE INGREDIENTS: Lactobacillus Acidophilus 16000000000 [CFU]/1 1; Bifidobacterium Animalis Lactis 15000000000 [CFU]/1 1
INACTIVE INGREDIENTS: Hydroxypropyl Cellulose, Unspecified; Silicon Dioxide; MAGNESIUM PALMITOSTEARATE

ProRiva

HEALTH CLAIM

71741-436-30
Dietary Supplement
Dispensed by Prescription

DESCRIPTION

ProRiva is an orally administered prescription probiotic dietary supplement.

STATEMENT OF IDENTITY

Supplement Facts
Serving size 1 Capsule
Amount per Serving: |  | % Daily Value
Lactobacillus Acidophilus | 16 Billion | [Daily value not established]
Bifidobacterium Animalis Lactis | 15 Billion

OTHER INGREDIENTS: Modified Cellulose, Silicon Dioxide, Magnesium Stearate.

Preservative Free and Gluten Free

INDICATIONS

ProRiva is an orally administered prescription probiotic formulation for the clinical dietary management of suboptimal nutritional status in patients where advanced supplementation is required and nutritional supplementation in physiologically stressful conditions for maintenance of good health is needed. ProRiva should be administered under the supervision of a licensed medical practitioner.

CONTRAINDICATIONS

This product is contraindicated in patients with a known hypersensitivity to any of the ingredients.

WARNING

ProRiva should only be used under the direction and supervision of a licensed medical practitioner. Use with caution in patients that may have a medical condition, are pregnant, lactating, trying to conceive, under the age of 18, or taking other medications.

ADVERSE REACTIONS

You should call your doctor for medical advice about serious adverse events. To report adverse side effects or to obtain product information, contact Redmont Pharmaceuticals, LLC at 1-800-986-5909.

DOSAGE AND ADMINISTRATION

Usual adult dose is 1 capsule once or twice daily or as prescribed by a licensed medical practitioner.

HOW SUPPLIED

Bottle of 30 capsules (71741-436-30 [Redmont Pharmaceuticals does not represent this product code to be National Drug Code (NDC). Product codes are formatted according to standard industry practice, to meet the formatting requirement by pedigree reporting and supply-chain control including pharmacies.]). Capsule is off-white, oblong.

STORAGE AND HANDLING

Store 15°- 30°C (59°-86°F) [See USP Controlled Room Temperature.] Avoid excessive heat, light, moisture and exceeding 85% humidity. Keep in a cool, dry place.

TAMPER EVIDENT

Do not use if seal is broken or missing.

HEALTH CLAIM

MADE IN USA

Distributed by:

Redmont Pharmaceuticals, LLC
Birmingham, AL 35209
800-986-5909

These statements have not been evaluated by the Food and Drug Administration. This product is not intended to diagnose, treat, cure, or prevent any diseases.

SAFE HANDLING WARNING

KEEP THIS AND ALL MEDICATIONS OUT OF THE REACH OF CHILDREN

HEALTH CLAIM

© 2025 Redmont Pharmaceuticals, LLC
436111-0925

PRINCIPAL DISPLAY PANEL - 30 Capsule Bottle Label

71741-436-30

ProRiva

PROBIOTIC SUPPORT

Lactobacillus Acidophilus
Bifidobacterium Animalis Lactis
31 Billion CFU's
DIETARY SUPPLEMENT

30 CAPSULES

Dispensed by Prescription